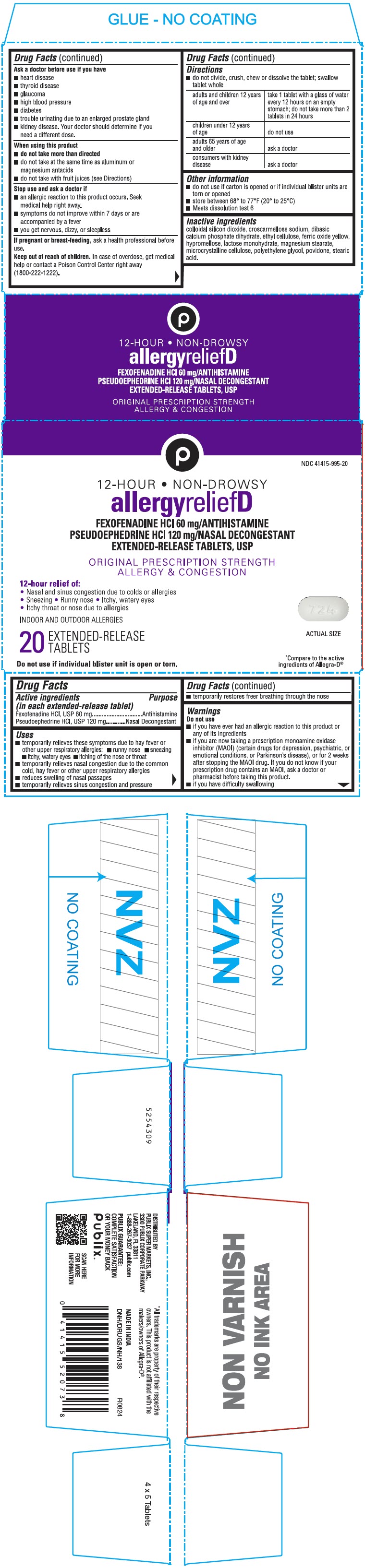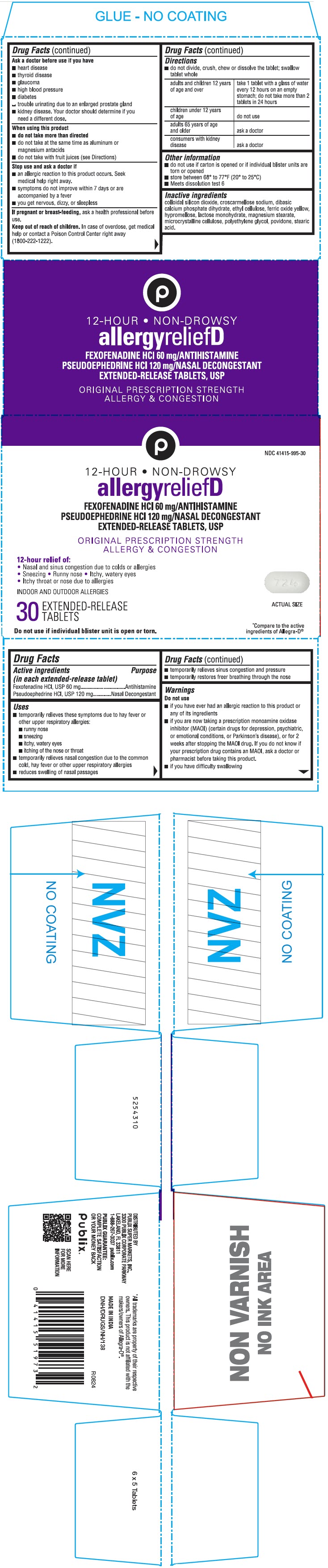 DRUG LABEL: Fexofenadine Hydrochloride and Pseudoephedrine Hydrochloride
NDC: 41415-995 | Form: TABLET, EXTENDED RELEASE
Manufacturer: PUBLIX SUPER MARKETS, INC
Category: otc | Type: HUMAN OTC DRUG LABEL
Date: 20241010

ACTIVE INGREDIENTS: FEXOFENADINE HYDROCHLORIDE 60 mg/1 1; PSEUDOEPHEDRINE HYDROCHLORIDE 120 mg/1 1
INACTIVE INGREDIENTS: LACTOSE MONOHYDRATE; MICROCRYSTALLINE CELLULOSE; CROSCARMELLOSE SODIUM; POVIDONE, UNSPECIFIED; MAGNESIUM STEARATE; DIBASIC CALCIUM PHOSPHATE DIHYDRATE; SILICON DIOXIDE; ETHYLCELLULOSE, UNSPECIFIED; FERRIC OXIDE YELLOW; STEARIC ACID; HYPROMELLOSE, UNSPECIFIED; POLYETHYLENE GLYCOL, UNSPECIFIED

Fexofenadine Hydrochloride and Pseudoephedrine Hydrochloride

Drug Facts

Active ingredients (in each extended-release tablet)

Fexofenadine HCl, USP 60 mg

Pseudoephedrine HCl, USP 120 mg

Purpose

Antihistamine

Nasal Decongestant

Uses

- temporarily relieves these symptoms due to hay fever or other upper respiratory allergies:
- runny nose
- sneezing
- itchy, watery eyes
- itching of the nose or throat
- temporarily relieves nasal congestion due to the common cold, hay fever or other upper respiratory allergies
- reduces swelling of nasal passages
- temporarily relieves sinus congestion and pressure
- temporarily restores freer breathing through the nose

Warnings

Do not use

- if you have ever had an allergic reaction to this product or any of its ingredients
- if you are now taking a prescription monoamine oxidase inhibitor (MAOI) (certain drugs for depression, psychiatric, or emotional conditions, or Parkinson's disease), or for 2 weeks after stopping the MAOI drug. If you do not know if your prescription drug contains an MAOI, ask a doctor or pharmacist before taking this product.
- if you have difficulty swallowing

Ask a doctor before use if you have

- heart disease
- thyroid disease
- glaucoma
- high blood pressure
- diabetes
- trouble urinating due to an enlarged prostate gland
- kidney disease. Your doctor should determine if you need a different dose.

When using this product

- do not take more than directed
- do not take at the same time as aluminum or magnesium antacids
- do not take with fruit juices (see Directions)

Stop use and ask a Doctor if

- an allergic reaction to this product occurs. Seek medical help right away.
- symptoms do not improve within 7 days or are accompanied by a fever
- you get nervous, dizzy, or sleepless

PREGNANCY OR BREAST FEEDING

If pregnant or breast feeding, ask a health professional before use.

In case of overdose, get medical help or contact a Poison Control Center right away (1800-222-1222)

Keep Out of Reach of Children.

Directions

- do not divide, crush, chew or dissolve the tablet; swallow tablet whole

adults and children 12 years of age and over | take 1 tablet with a glass of water every 12 hours on an empty stomach; do not take more than 2 tablets in 24 hours
children under 12 years of age | do not use
adults 65 years of age and older | ask a doctor
consumers with kidney disease | ask a doctor

Other information

- do not use if carton is opened or if individual blister units are torn or opened
- store between 68° to 77°F (20° to 25 °C)
- Meets dissolution test 6

Inactive ingredients

colloidal silicon dioxide, croscarmellose sodium, dibasic calcium phosphate dihydrate, ethyl cellulose, ferric oxide yellow, hypromellose, lactose monohydrate, magnesuim stearate, microcrystalline cellulose, polyethylene glycol, povidone, stearic acid.

DISTRIBUTED BY
PUBLIX SUPER MARKETS, INC.,
3300 PUBLIX CORPORATE PARKWAY
LAKELAND, FL 33811

PRINCIPAL DISPLAY PANEL - 20 Tablet Blister Pack Carton

NDC 41415-995-20

12-HOUR • NON-DROWSY

allergyreliefD

FEXOFENADINE HCl 60 mg/ANTIHISTAMINE
PSEUDOEPHEDRINE HCl 120 mg/NASAL DECONGESTANT
EXTENDED-RELEASE TABLETS, USP

ORIGINAL PRESCRIPTION STRENGTH
ALLERGY & CONGESTION

12-hour relief of:
• Nasal and sinus congestion due to colds or allergies
• Sneezing • Runny nose • Itchy, watery eyes
• Itchy throat or nose due to allergies

INDOOR AND OUTDOOR ALLERGIES

20
EXTENDED-RELEASE
TABLETS

ACTUAL SIZE

*Compare to the active
ingredients of Allegra-D®

Do not use if individual blister unit is open or torn.

PRINCIPAL DISPLAY PANEL - 30 Tablet Blister Pack Carton

NDC 41415-995-30

12-HOUR • NON-DROWSY

allergyreliefD

FEXOFENADINE HCl 60 mg/ANTIHISTAMINE
PSEUDOEPHEDRINE HCl 120 mg/NASAL DECONGESTANT
EXTENDED-RELEASE TABLETS, USP

ORIGINAL PRESCRIPTION STRENGTH
ALLERGY & CONGESTION

12-hour relief of:
• Nasal and sinus congestion due to colds or allergies
• Sneezing • Runny nose • Itchy, watery eyes
• Itchy throat or nose due to allergies

INDOOR AND OUTDOOR ALLERGIES

30
EXTENDED-RELEASE
TABLETS

ACTUAL SIZE

*Compare to the active
ingredients of Allegra-D®

Do not use if individual blister unit is open or torn.